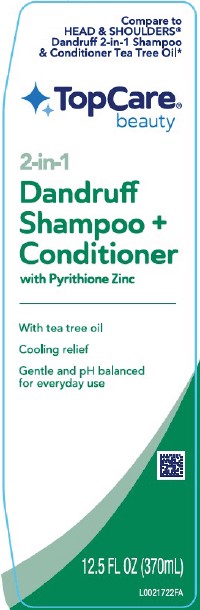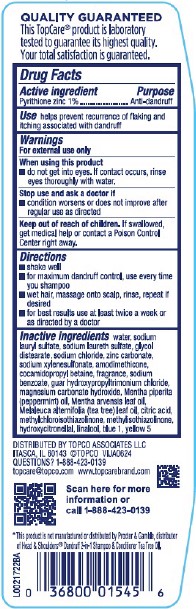 DRUG LABEL: Pyrithione zinc
NDC: 76162-970 | Form: SHAMPOO
Manufacturer: Topco Associates LLC
Category: otc | Type: HUMAN OTC DRUG LABEL
Date: 20260213

ACTIVE INGREDIENTS: PYRITHIONE ZINC 10 mg/1 mL
INACTIVE INGREDIENTS: WATER; SODIUM LAURYL SULFATE; SODIUM LAURETH SULFATE; GLYCOL DISTEARATE; SODIUM CHLORIDE; ZINC CARBONATE; SODIUM XYLENESULFONATE; AMODIMETHICONE (800 CST); COCAMIDOPROPYL BETAINE; SODIUM BENZOATE; GUAR HYDROXYPROPYLTRIMONIUM CHLORIDE (1.7 SUBSTITUENTS PER SACCHARIDE); MAGNESIUM CARBONATE HYDROXIDE; PEPPERMINT OIL; MENTHA ARVENSIS LEAF OIL; TEA TREE OIL; CITRIC ACID MONOHYDRATE; METHYLCHLOROISOTHIAZOLINONE; METHYLISOTHIAZOLINONE; HYDROXYCITRONELLAL; LINALOOL, (+/-)-; FD&C BLUE NO. 1; FD&C YELLOW NO. 5

Top Care 470.000/470AB
Tea Tree 2 in 1 Dandruff Shampoo and Conditioner

claims

QUALITY GUARANTEED

This TopCare®product is laboratory tested to guarantee its highest quality.

Your total satisfaction is guaranteed.

Active ingredient

Pyrithione Zinc 1%

Purpose

Anti-dandruff

Use

helps prevent recurrence of flaking and itching associated with dandruff

Warnings

For external use only

When using this product

- do not get into eyes. If contact occurs, rinse eyes thoroughly with water.

Stop use and ask a doctor if

- condition worsens or does not improve after regular use as directed

Keep out of reach of children.

If swallowed, get medical help or contact a Poison Control Center right away.

Directions

- shake well
- for maximum dandruff control, use every time you shampoo
- wet hair, massage onto scalp, rinse, repeat if desired
- for best results use at least twice a week or as directed by a doctor

inactive ingredients

water, sodium lauryl sulfate, sodium laureth sulfate, glycol distearate, sodium chloride, zinc carbonate, sodium xylenesulfonate, amodimethicone, cocamidopropyl betaine, fragrance, sodium benzoate, guar hydroxypropyltrimonium chloride, magnesium carbonate hydroxide, Mentha piperita (peppermint) oil, Mentha arvensis leaf oil, Melaleuca alternifolia (tea tree) leaf oil, citric acid, methylchloroisothiazolinone, methylisothiazolinone, hydroxycitronellal, linalool, blue 1, yellow 5

Adverse Reactions

DISTRIBUTED BY TOPCO ASSOCIATES LLC

ITASCA, IL 60143 ©TOPCO VIJA0624

QUESTIONS? 1-888-423-0139

topcare@topco.com www.topcarebrand.com

Scan here for more information or call 1-888-423-0139

Disclaimer

*This product is not manufactured or distributed by Procter & Gamble, distributor of Head & Shoulders®Dandruff 2-in-1 Shampoo & Conditioner Tea Tree Oil.

Principal display panel

Compare to HEAD & SHOULDERS®Dandruff 2-in-1 Shampoo & Conditioner Tea Tree Oil*

Top Care®

beauty

2-in-1

Dandruff Shampoo + Conditioner

with Pyrithione Zinc

With tea tree oil

Cooling relief

Gentle and pH balanced for everyday use

12.5 FL OZ (370 mL)